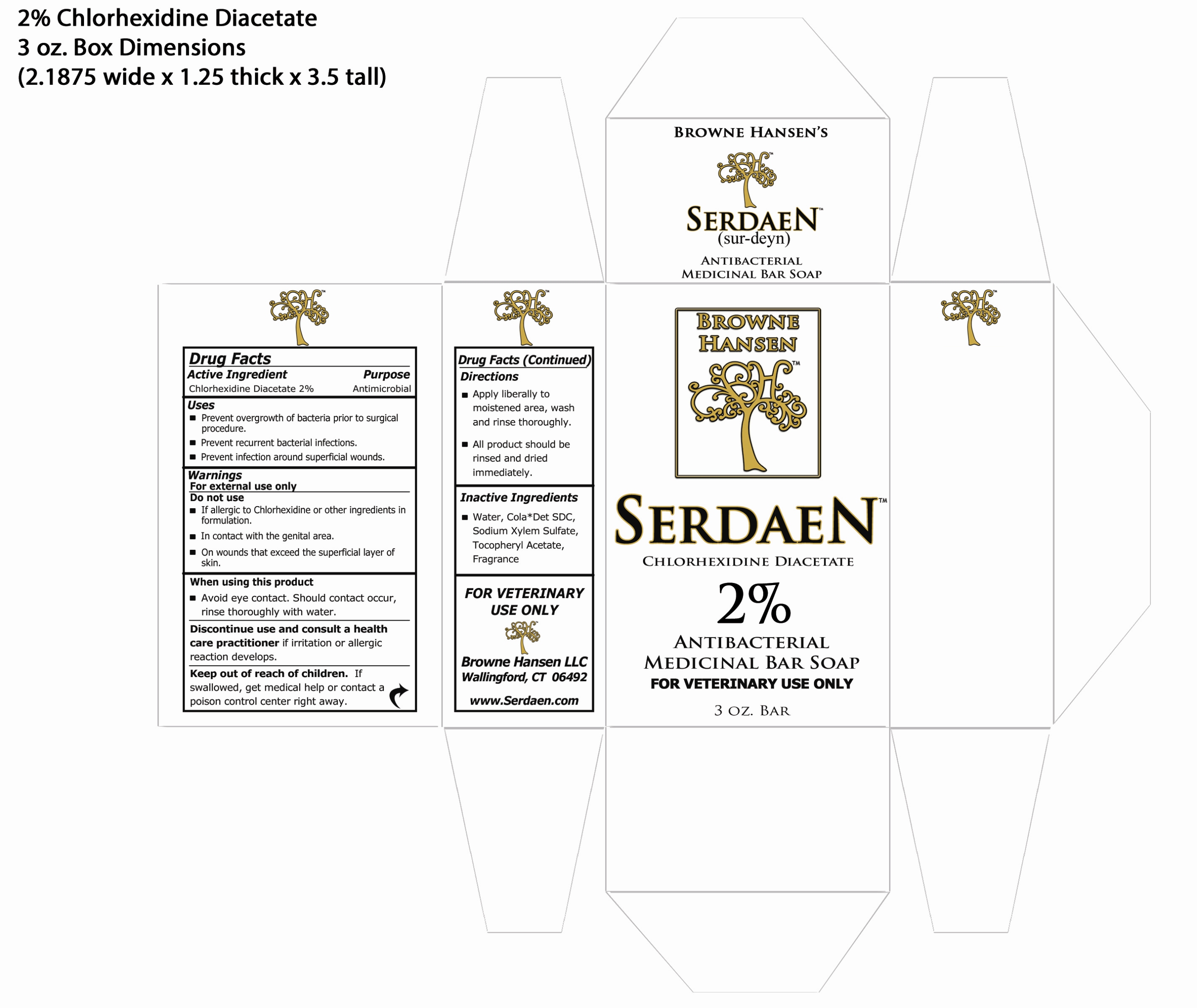 DRUG LABEL: Serdaen
NDC: 56149-600 | Form: SOAP
Manufacturer: Browne Hansen LLC
Category: animal | Type: OTC ANIMAL DRUG LABEL
Date: 20130629

ACTIVE INGREDIENTS: CHLORHEXIDINE ACETATE 48 mg/3 g
INACTIVE INGREDIENTS: WATER; SODIUM SULFATE; .ALPHA.-TOCOPHEROL ACETATE; DIPROPYLENE GLYCOL; MONOETHANOLAMINE

Drug Facts

Active Ingredient
Chlorhexidine Diacetate 1%

Inactive Ingredients
Water, Cola Det SDC, Sodium Xylem Sulfate, Tocopheryl Acetate, Fragrance

Purpose
Antimicrobial

Uses
Prevent overgrowth of bacteria prior to surgical procedure
Prevent recurrent bacterial infections
Prevent infections around superficial wounds

Keep out of reach of children. If swallowed, get medical help
or contact a poison control center right away.

Warnings
For external use only.
Do not use:
If allergic to Chlorhexidine or other ingredients in formulation
In contact with the genital area
On wounds that exceed the superficial layer of skin.

When using this product
Avoid eye contact. Should contact occur,
rinse thoroughly with water.

Discontinue use and consult a health care practitioner
if irritation or allergic reaction develops.

Directions
Apply liberally to moistened area, wash and rinse thoroughly.
All product should be rinsed and dried immediately